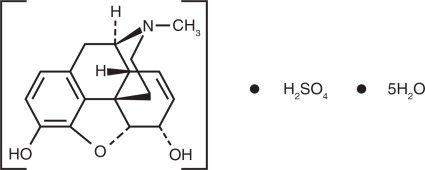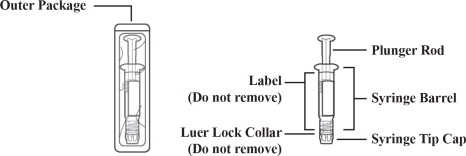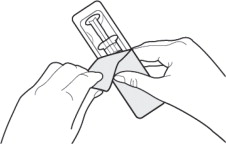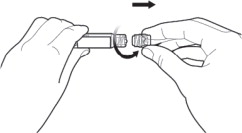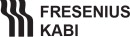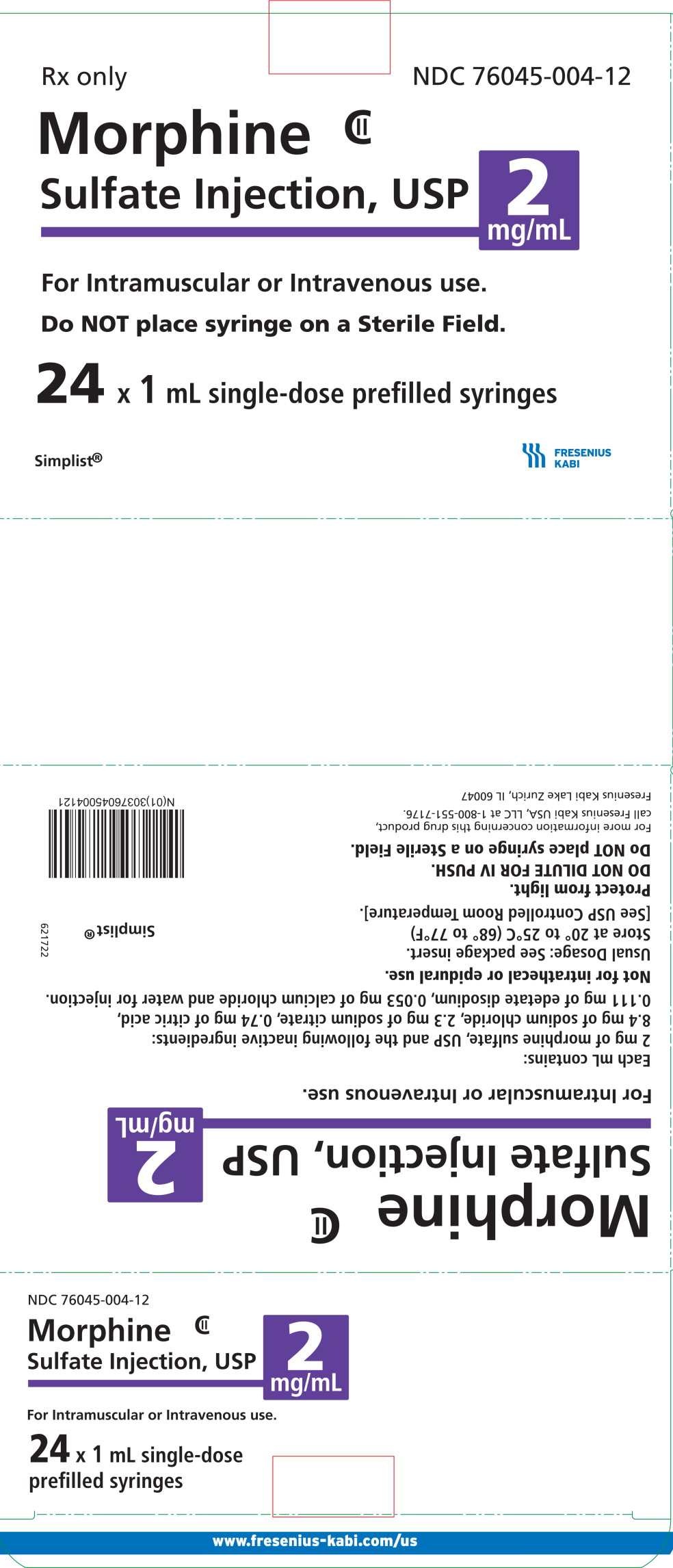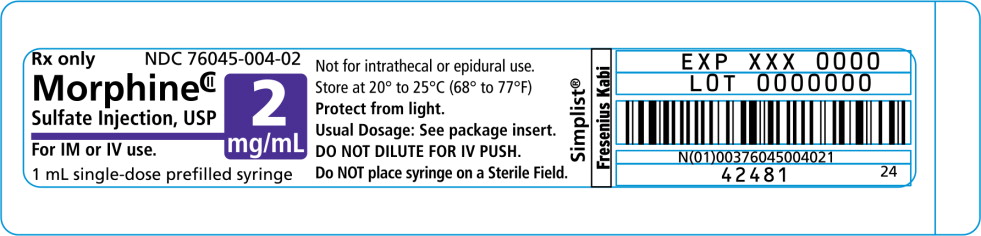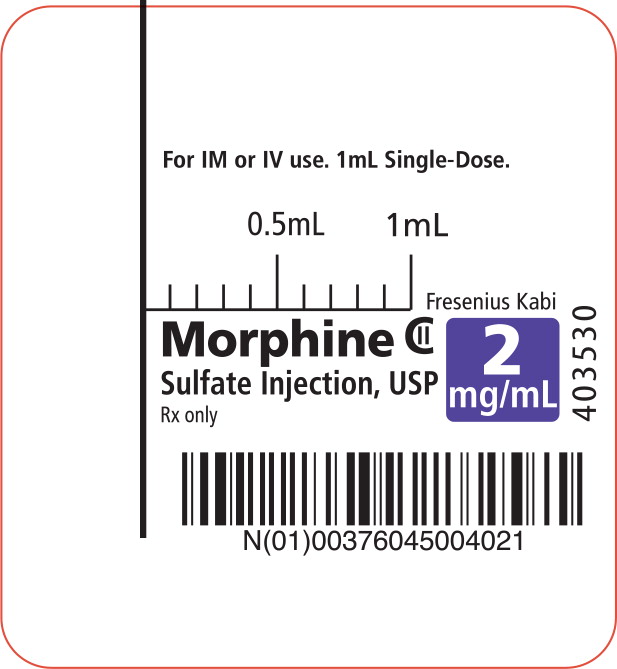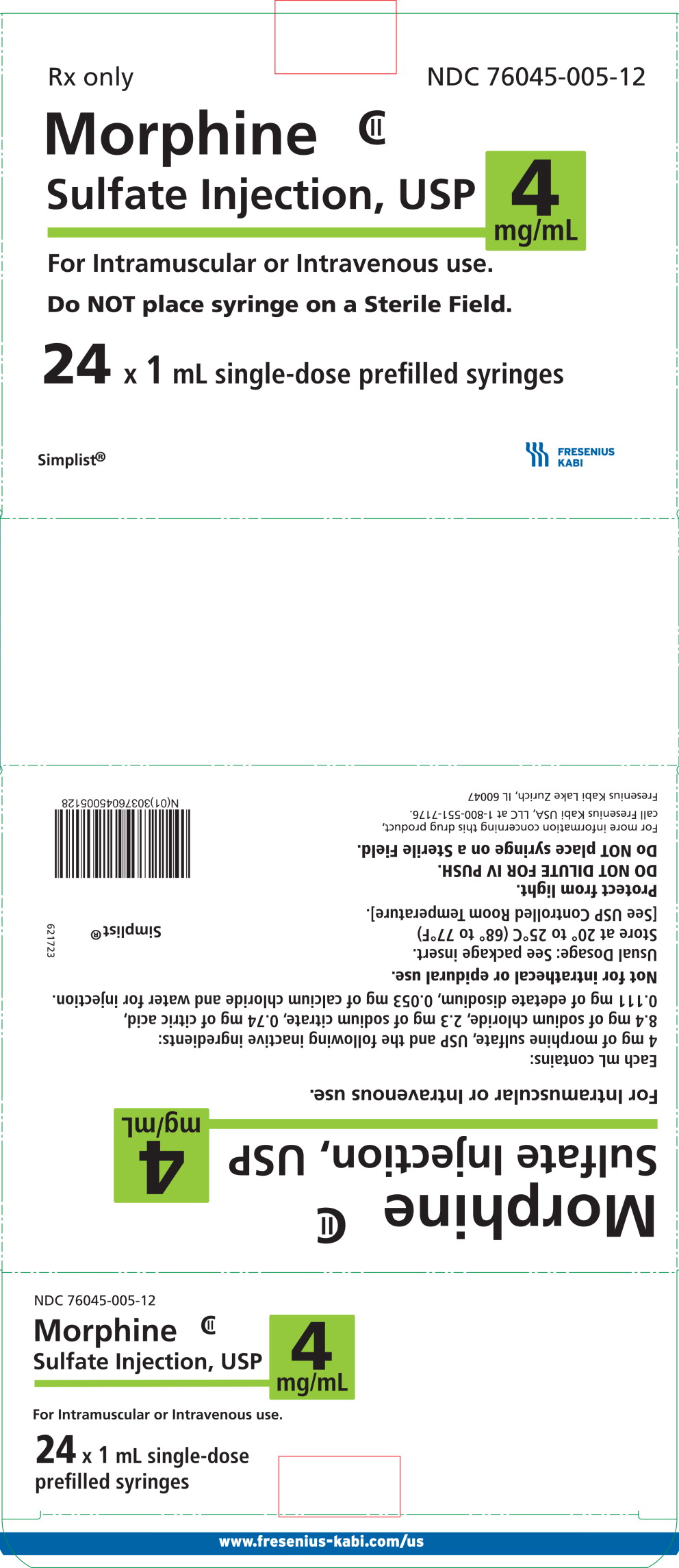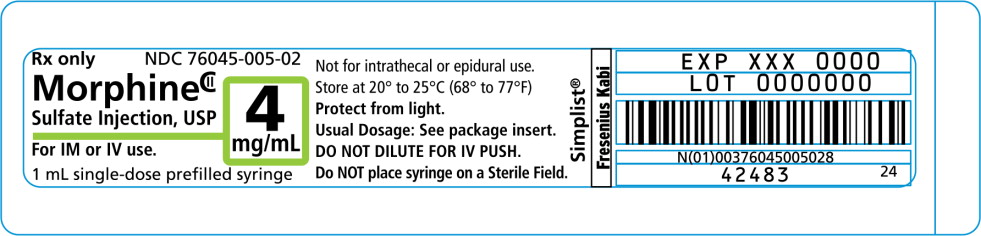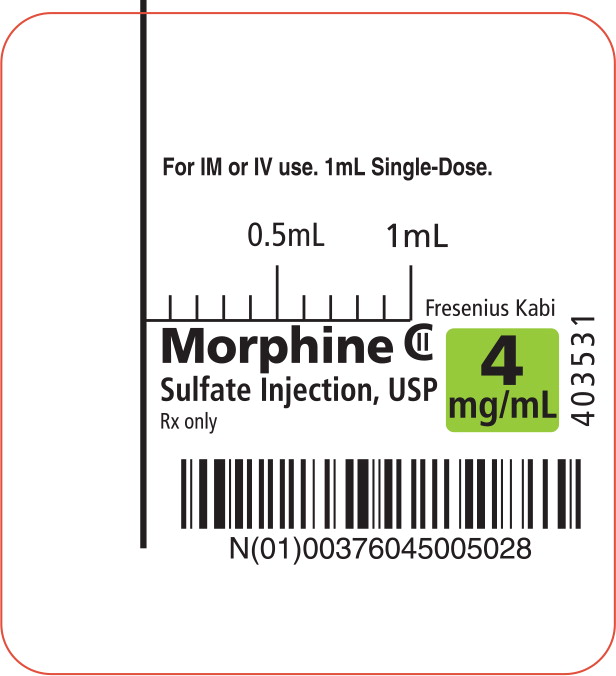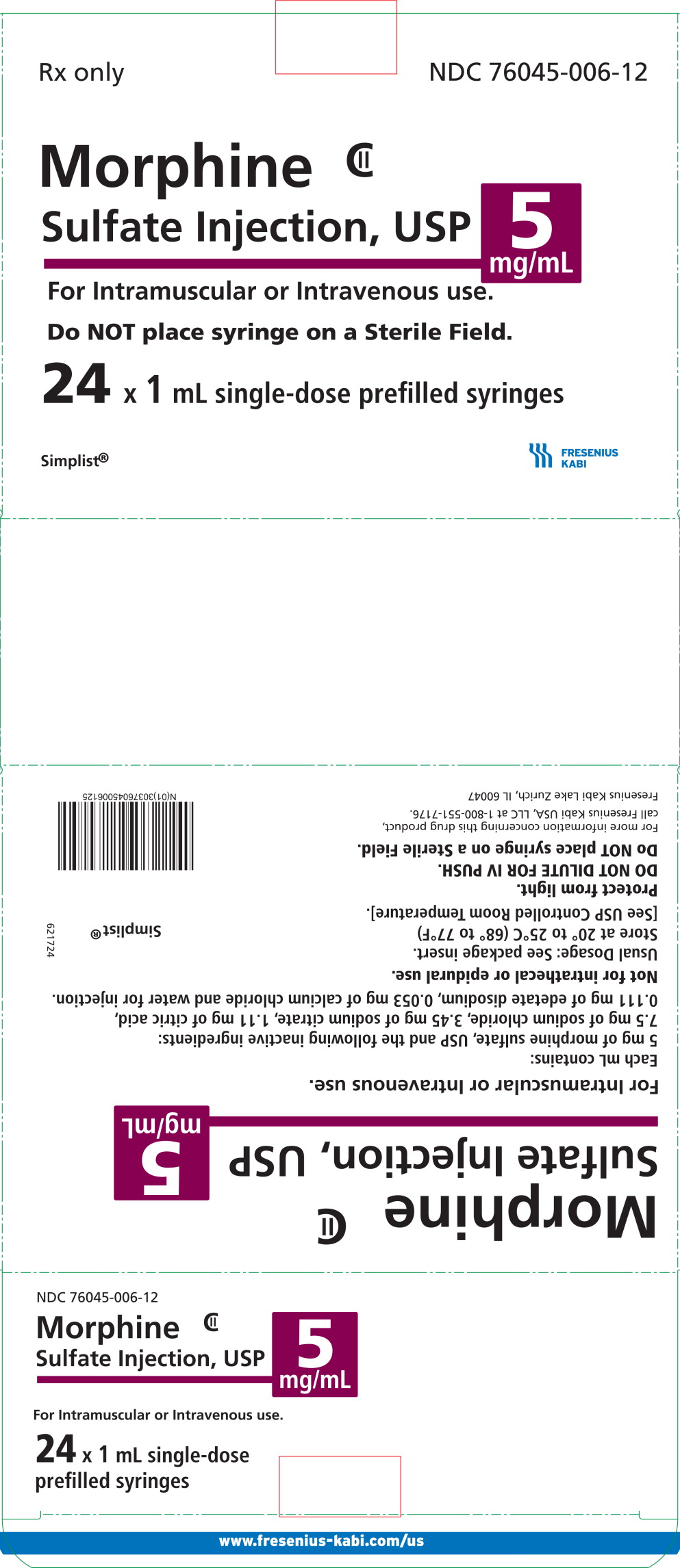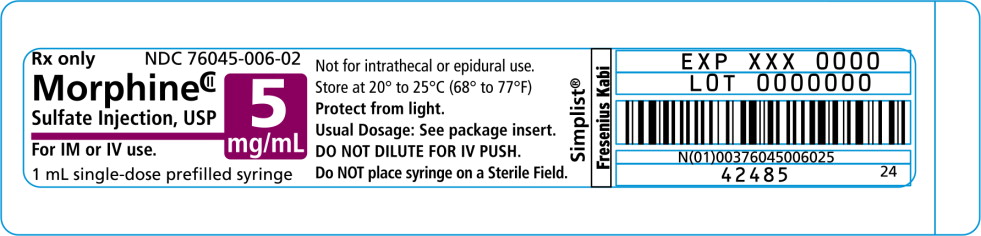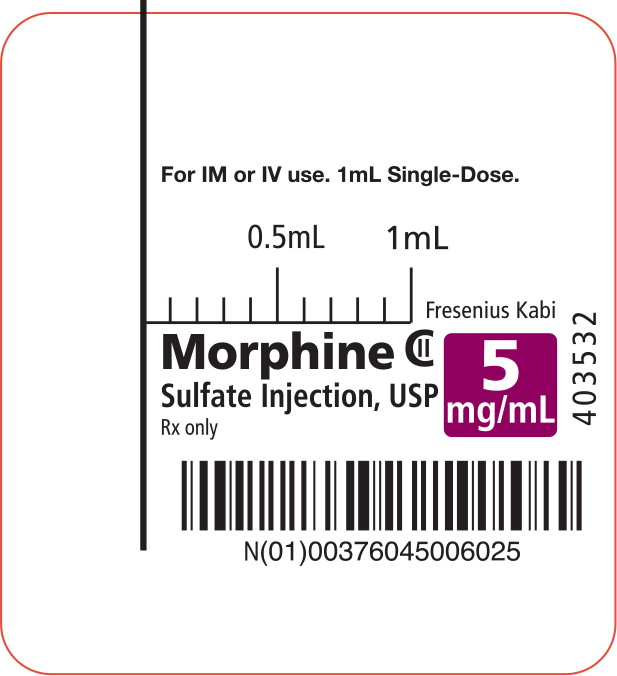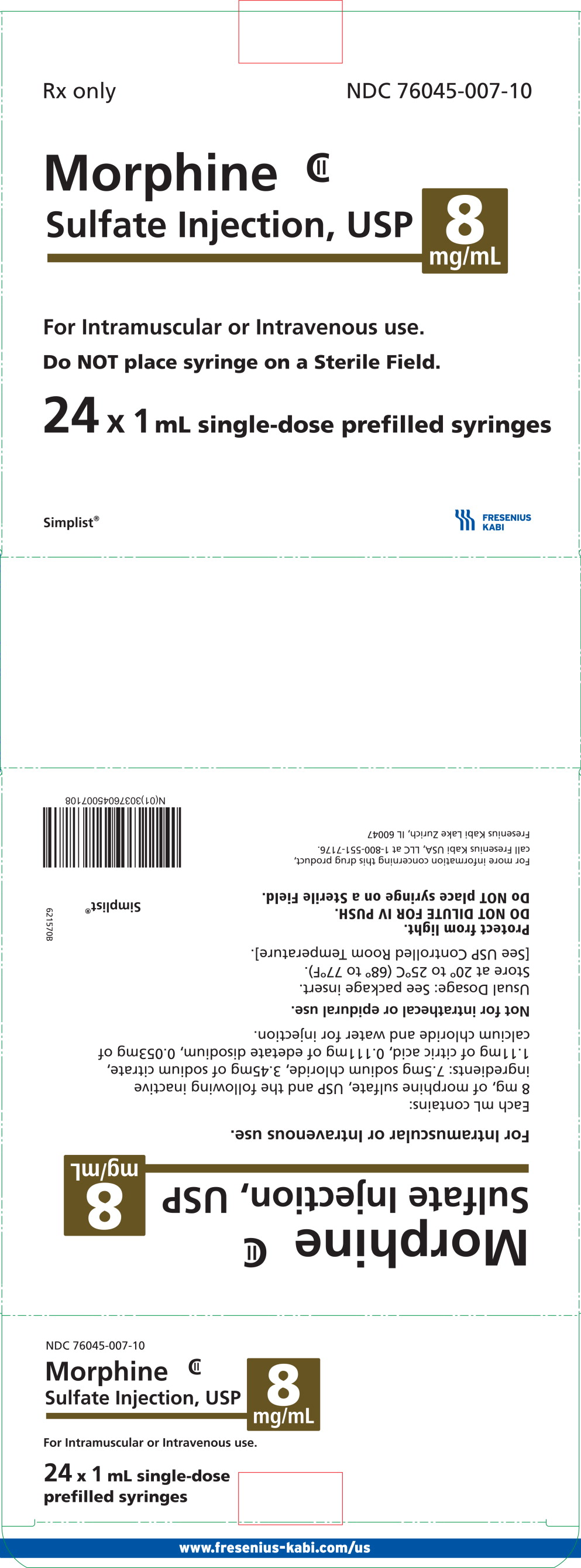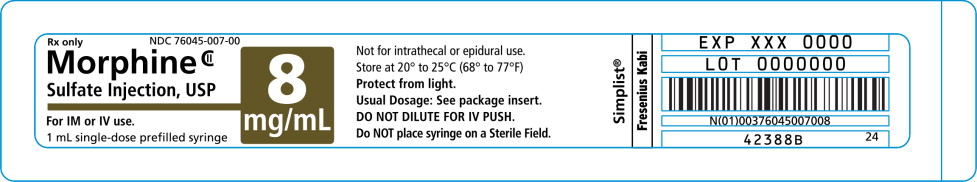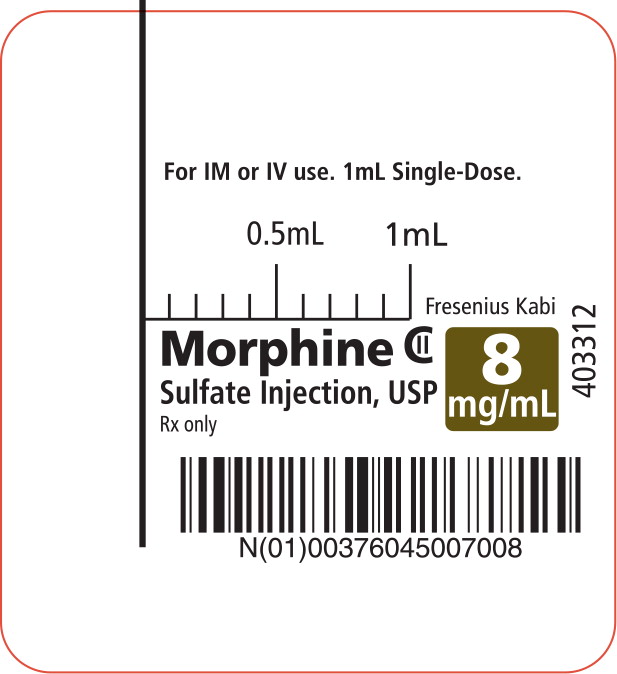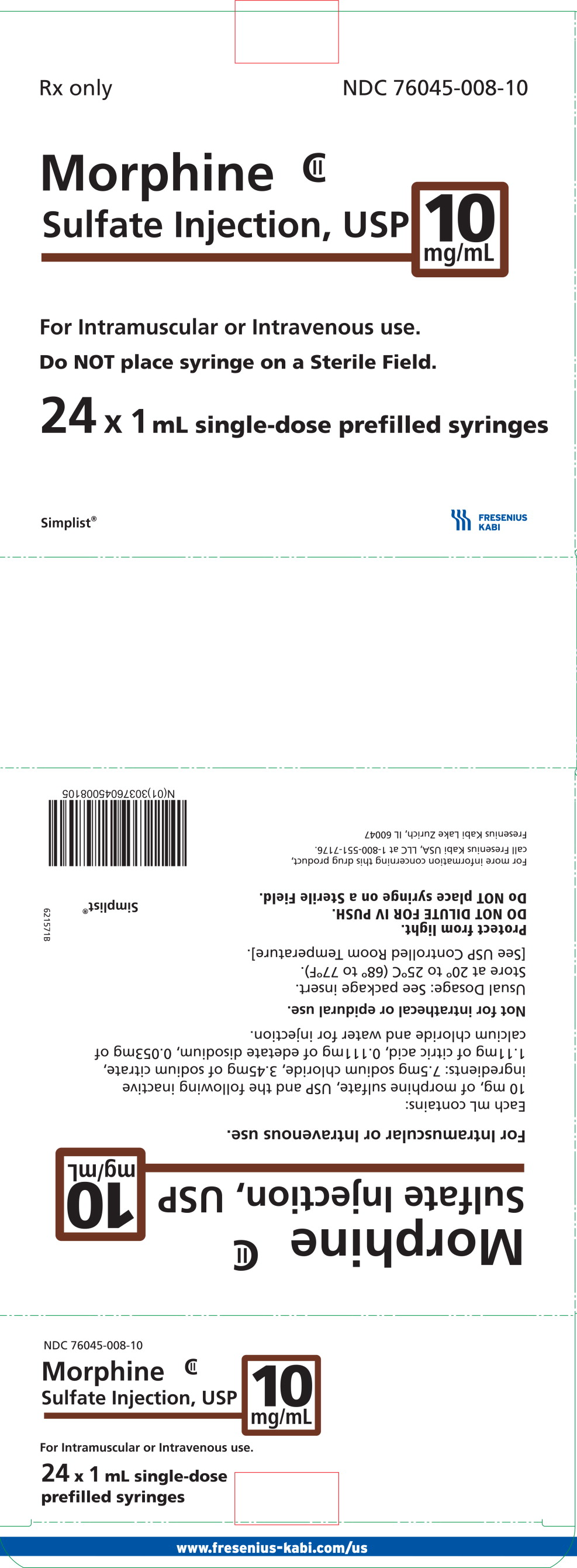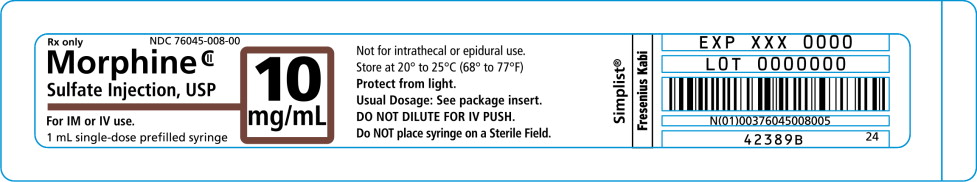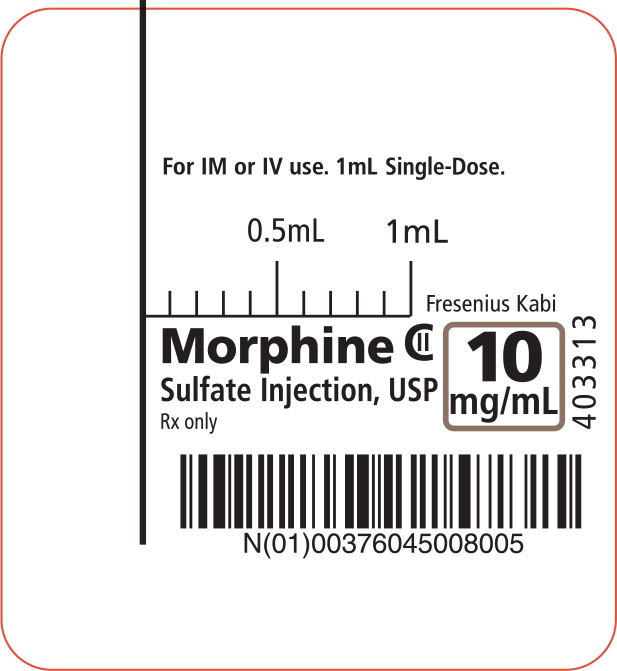 DRUG LABEL: Morphine Sulfate
NDC: 76045-004 | Form: INJECTION, SOLUTION
Manufacturer: Fresenius Kabi USA, LLC
Category: prescription | Type: HUMAN PRESCRIPTION DRUG LABEL
Date: 20250904
DEA Schedule: CII

ACTIVE INGREDIENTS: MORPHINE SULFATE 2 mg/1 mL
INACTIVE INGREDIENTS: SODIUM CHLORIDE; TRISODIUM CITRATE DIHYDRATE; CITRIC ACID MONOHYDRATE; EDETATE DISODIUM; CALCIUM CHLORIDE; WATER

HIGHLIGHTS OF PRESCRIBING INFORMATION

These highlights do not include all the information needed to use MORPHINE SULFATE INJECTION safely and effectively. See full prescribing information for MORPHINE SULFATE INJECTION.
Morphine Sulfate injection, for intravenous or intramuscular use, CII
Initial U.S. Approval: 1941

RECENT MAJOR CHANGES

Warnings and Precautions | 10/2019

WARNING: ADDICTION, ABUSE, AND MISUSE; LIFE-THREATENING RESPIRATORY DEPRESSION; NEONATAL OPIOID WITHDRAWAL SYNDROME; and RISKS FROM CONCOMITANT USE WITH BENZODIAZEPINES OR OTHER CNS DEPRESSANTS

See full prescribing information for complete boxed warning.

- Morphine Sulfate Injection exposes users to risks of addiction, abuse, and misuse, which can lead to overdose and death. Assess patient's risk before prescribing and monitor regularly for these behaviors and conditions. (5.1)
- Serious, life-threatening, or fatal respiratory depression may occur. Monitor closely, especially upon initiation or following a dose increase. (5.2)
- Prolonged use of Morphine Sulfate Injection during pregnancy can result in neonatal opioid withdrawal syndrome, which may be life-threatening if not recognized and treated. If prolonged opioid use is required in a pregnant woman, advise the patient of the risk of neonatal opioid withdrawal syndrome and ensure that appropriate treatment will be available. (5.3)
- Concomitant use of opioids with benzodiazepines or other central nervous system (CNS) depressants, including alcohol, may result in profound sedation, respiratory depression, coma, and death. Reserve concomitant prescribing for use in patients for whom alternative treatment options are inadequate; limit dosages and durations to the minimum required; and follow patients for signs and symptoms of respiratory depression and sedation. (5.4, 7)

1 INDICATIONS AND USAGE

Morphine Sulfate Injection is an opioid agonist indicated for the management of pain severe enough to require an opioid analgesic and for which alternative treatments are inadequate. (1)

Limitations of Use (1)

Because of the risks of addiction, abuse, and misuse with opioids, even at recommended doses, reserve Morphine Sulfate Injection, for use in patients for whom alternative treatment options [e.g., non-opioid analgesics or opioid combination products]:

- Have not been tolerated, or are not expected to be tolerated
- Have not provided adequate analgesia, or are not expected to provide adequate analgesia

2 DOSAGE AND ADMINISTRATION

- Use the lowest effective dosage for the shortest duration consistent with individual patient treatment goals. (2.1)
- Individualize dosing based on the severity of pain, patient response, prior analgesic experience, and risk factors for addiction, abuse, and misuse. (2.1)
- Direct Intravenous Injection: Initiate treatment with 0.1 mg to 0.2 mg per kg every 4 hours as needed to manage pain. (2.2)
- Intramuscular Injection: Initiate treatment with 10 mg, every 4 hours as needed to manage pain (based on a 70 kg adult). (2.2)
- Do not stop Morphine Sulfate Injection abruptly in a physically dependent patient. (2.4)

3 DOSAGE FORMS AND STRENGTHS

Injection, 2 mg/mL, 4 mg/mL, 5 mg/mL, 8 mg/mL, and 10 mg/mL in a single-dose prefilled syringe for intravenous or intramuscular use. (3)

4 CONTRAINDICATIONS

- Significant respiratory depression. (4)
- Acute or severe bronchial asthma in an unmonitored setting or in absence of resuscitative equipment. (4)
- Concurrent use of monoamine oxidase inhibitors (MAOIs) or use of MAOIs within the last 14 days (4)
- Known or suspected gastrointestinal obstruction, including paralytic ileus. (4)
- Hypersensitivity to morphine. (4)

5 WARNINGS AND PRECAUTIONS

- Cardiovascular Instability: High doses are excitatory. Have Naloxone Injection and resuscitative equipment immediately available. (5.5)
- Life-Threatening Respiratory Depression in Patients with Chronic Pulmonary Disease or in Elderly, Cachectic, or Debilitated Patients: Monitor closely, particularly during initiation and titration. (5.2)
- Adrenal Insufficiency: If diagnosed, treat with physiologic replacement of corticosteroids, and wean patient off of the opioid. (5.8)
- Severe Hypotension: Monitor during dosage initiation and titration. Avoid use of Morphine Sulfate Injection in patients with circulatory shock. (5.9)
- Risks of Use in Patients with Increased Intracranial Pressure, Brain Tumors, Head Injury, or Impaired Consciousness: Monitor for sedation and respiratory depression. Avoid use of Morphine Sulfate Injection in patients with impaired consciousness or coma. (5.10)

6 ADVERSE REACTIONS

The most serious adverse reactions encountered are respiratory depression, apnea, circulatory depression, respiratory arrest, shock and cardiac arrest. Other common frequently observed adverse reactions include: sedation, lightheadedness, dizziness, nausea, vomiting, constipation and diaphoresis. (6)

To report SUSPECTED ADVERSE REACTIONS, contact Fresenius Kabi USA, LLC at 1-800-551-7176 or FDA at 1-800-FDA-1088 or www.fda.gov/medwatch

7 DRUG INTERACTIONS

- Serotonergic Drugs: Concomitant use may result in serotonin syndrome. Discontinue Morphine Sulfate Injection if serotonin syndrome is suspected. (7)
- Mixed Agonist/Antagonist and Partial Agonist Opioid Analgesics: Avoid use with Morphine Sulfate Injection because they may reduce analgesic effect of Morphine Sulfate Injection or precipitate withdrawal symptoms. (7)

8 USE IN SPECIFIC POPULATIONS

Pregnancy: May cause fetal harm. (8.1)

FULL PRESCRIBING INFORMATION

WARNING: ADDICTION, ABUSE, AND MISUSE; LIFE-THREATENING RESPIRATORY DEPRESSION; NEONATAL OPIOID WITHDRAWAL SYNDROME; and RISKS FROM CONCOMITANT USE WITH BENZODIAZEPINES OR OTHER CNS DEPRESSANTS

Addiction, Abuse, and Misuse

Morphine Sulfate Injection exposes patients and other users to the risks of opioid addiction, abuse, and misuse, which can lead to overdose and death. Assess each patient's risk prior to prescribing Morphine Sulfate Injection, and monitor all patients regularly for the development of these behaviors and conditions [see Warnings and Precautions (5.1)].

Life-Threatening Respiratory Depression

Serious, life-threatening, or fatal respiratory depression may occur with use of Morphine Sulfate Injection. Monitor for respiratory depression, especially during initiation of Morphine Sulfate Injection, or following a dose increase. Because of delay in maximum CNS effect with intravenously administered morphine (30 min), rapid IV administration may result in overdosing [see Warnings and Precautions (5.2)].

Neonatal Opioid Withdrawal Syndrome

Prolonged use of Morphine Sulfate Injection during pregnancy can result in neonatal opioid withdrawal syndrome, which may be life-threatening if not recognized and treated, and requires management according to protocols developed by neonatology experts. If opioid use is required for a prolonged period in a pregnant woman, advise the patient of the risk of neonatal opioid withdrawal syndrome and ensure that appropriate treatment will be available [see Warnings and Precautions (5.3)].

Risks From Concomitant Use With Benzodiazepines Or Other CNS Depressants

Concomitant use of opioids with benzodiazepines or other central nervous system (CNS) depressants, including alcohol, may result in profound sedation, respiratory depression, coma, and death [see Warnings and Precautions (5.4), Drug Interactions (7)].

- Reserve concomitant prescribing of Morphine Sulfate Injection and benzodiazepines or other CNS depressants for use in patients for whom alternative treatment options are inadequate.
- Limit dosages and durations to the minimum required.
- Follow patients for signs and symptoms of respiratory depression and sedation.

1 INDICATIONS AND USAGE

Morphine Sulfate Injection is indicated for the management of pain severe enough to require an opioid analgesic and for which alternative treatments are inadequate.

Limitations of Use

Because of the risks of addiction, abuse, and misuse with opioids, even at recommended doses [see Warnings and Precautions (5.1)], reserve Morphine Sulfate Injection for use in patients for whom alternative treatment options [e.g., non-opioid analgesics or opioid combination products]:

- Have not been tolerated, or are not expected to be tolerated
- Have not provided adequate analgesia, or are not expected to provide adequate analgesia

2 DOSAGE AND ADMINISTRATION

2.1 Important Dosage and Administration Instructions

Morphine Sulfate Injection is intended for intravenous and intramuscular administration.

Morphine Sulfate Injection is available in five concentrations for direct injection. Dosing errors can result in accidental overdose and death. Avoid dosing errors that may result from confusion between mg and mL and confusion with morphine injections of different concentrations when prescribing, dispensing, and administering Morphine Sulfate Injection. Ensure that the dose is communicated and dispensed accurately.

Use the lowest effective dosage for the shortest duration consistent with individual patient treatment goals [see Warnings and Precautions (5.1)].

Initiate the dosing regimen for each patient individually, taking into account the patient's severity of pain, patient response, prior analgesic treatment experience, and risk factors for addiction, abuse, and misuse [see Warnings and Precautions (5.1)].

Monitor patients closely for respiratory depression, especially within the first 24-72 hours of initiating therapy and following dosage increases with Morphine Sulfate Injection and adjust the dosage accordingly [see Warnings and Precautions (5.2)].

Administration of Morphine Sulfate Injection should be limited to use by those familiar with the management of respiratory depression. Morphine must be injected slowly; rapid intravenous administration may result in chest wall rigidity.

Inspect Morphine Sulfate Injection for particulate matter and discoloration prior to administration.

2.2 Initial Dosage

Direct Intravenous Injection

The usual starting dose in adults is 0.1 mg to 0.2 mg per kg every 4 hours as needed to manage pain. Administer the injection slowly.

Intramuscular Injection

The initial IM dose is 10 mg every 4 hours as needed to manage pain (based on a 70 kg adult).

2.3 Titration and Maintenance of Therapy

Individually titrate Morphine Sulfate Injection to a dose that provides adequate analgesia and minimizes adverse reactions. Continually reevaluate patients receiving Morphine Sulfate Injection to assess the maintenance of pain control and the relative incidence of adverse reactions, as well as monitoring for the development of addiction, abuse, or misuse [see Warnings and Precautions (5.1)].

If unacceptable opioid-related adverse reactions are observed, consider reducing the dosage. Adjust the dosage to obtain an appropriate balance between management of pain and opioid-related adverse reactions.

2.4 Discontinuation of Morphine Sulfate Injection

When a patient who has been taking Morphine Sulfate Injection regularly and may be physically dependent or no longer requires therapy with Morphine Sulfate Injection, taper the dose gradually, by 25% to 50% every 2 to 4 days, while monitoring carefully for signs and symptoms of withdrawal. If the patient develops these signs or symptoms, raise the dose to the previous level and taper more slowly, either by increasing the interval between decreases, decreasing the amount of change in dose, or both. Do not abruptly discontinue Morphine Sulfate Injection in a physically dependent patient [see Warnings and Precautions (5.13), Drug Abuse and Dependence (9.3)].

3 DOSAGE FORMS AND STRENGTHS

Morphine Sulfate Injection is available in the following strengths for intravenous (IV) and intramuscular (IM) administration.

2 mg/mL in 1 mL single-dose prefilled syringe for IV or IM use.
4 mg/mL in 1 mL single-dose prefilled syringe for IV or IM use.
5 mg/mL in 1 mL single-dose prefilled syringe for IV or IM use.
8 mg/mL in 1 mL single-dose prefilled syringe for IV or IM use.
10 mg/mL in 1 mL single-dose prefilled syringe for IV or IM use.

4 CONTRAINDICATIONS

Morphine Sulfate Injection is contraindicated in patients with:

- Significant respiratory depression [see Warnings and Precautions (5.2)]
- Acute or severe bronchial asthma in an unmonitored setting or in the absence of resuscitative equipment [see Warnings and Precautions (5.6)]
- Concurrent use of monoamine oxidase inhibitors (MAOIs) or use of MAOIs within the last 14 days [see Warnings and Precautions (5.7)].
- Known or suspected gastrointestinal obstruction, including paralytic ileus [see Warnings and Precautions (5.11)]
- Hypersensitivity to morphine (e.g., anaphylaxis) [see Adverse Reactions (6)]

5 WARNINGS AND PRECAUTIONS

5.1 Addiction, Abuse, and Misuse

Morphine Sulfate Injection contains morphine, a Schedule II controlled substance. As an opioid, Morphine Sulfate Injection exposes users to the risks of addiction, abuse, and misuse [see Drug Abuse and Dependence (9)].

Although the risk of addiction in any individual is unknown, it can occur in patients appropriately prescribed Morphine Sulfate Injection. Addiction can occur at recommended dosages and if the drug is misused or abused.

Assess each patient's risk for opioid addiction, abuse, or misuse prior to prescribing Morphine Sulfate Injection, and monitor all patients receiving Morphine Sulfate Injection for the development of these behaviors and conditions. Risks are increased in patients with a personal or family history of substance abuse (including drug or alcohol abuse or addiction) or mental illness (e.g., major depression). The potential for these risks should not, however, prevent the proper management of pain in any given patient. Patients at increased risk may be prescribed opioids such as Morphine Sulfate Injection, but use in such patients necessitates intensive counseling about the risks and proper use of Morphine Sulfate Injection, along with intensive monitoring for signs of addiction, abuse, and misuse.

Opioids are sought by drug abusers and people with addiction disorders and are subject to criminal diversion. Consider these risks when prescribing or dispensing Morphine Sulfate Injection. Strategies to reduce these risks include prescribing the drug in the smallest appropriate quantity. Contact local state professional licensing board or state controlled substances authority for information on how to prevent and detect abuse or diversion of this product.

5.2 Life-Threatening Respiratory Depression

Serious, life-threatening, or fatal respiratory depression has been reported with the use of opioids, even when used as recommended. Respiratory depression, if not immediately recognized and treated, may lead to respiratory arrest and death. Management of respiratory depression may include close observation, supportive measures, and use of opioid antagonists, depending on the patient's clinical status [see Overdosage (10)]. Carbon dioxide (CO2) retention from opioid-induced respiratory depression can exacerbate the sedating effects of opioids.

While serious, life-threatening, or fatal respiratory depression can occur at any time during the use of Morphine Sulfate Injection, the risk is greatest during the initiation of therapy or following a dosage increase. Because of a delay in the maximum CNS effect with intravenously administered Morphine Sulfate Injection (30 min), rapid administration may result in overdosing. The respiratory depression may be severe and could require intervention [see OVERDOSAGE (10)]. Monitor patients closely for respiratory depression, especially within the first 24-72 hours of initiating therapy with and following dosage increases of Morphine Sulfate Injection.

To reduce the risk of respiratory depression, proper dosing and titration of Morphine Sulfate Injection, are essential [see Dosage and Administration (2.4)]. Overestimating the Morphine Sulfate Injection, dosage when converting patients from another opioid product can result in a fatal overdose with the first dose.

Opioids can cause sleep-related breathing disorders including central sleep apnea (CSA) and sleep-related hypoxemia. Opioid use increases the risk of CSA in a dose-dependent fashion. In patients who present with CSA, consider decreasing the opioid dosage using best practices for opioid taper [see Dosage and Administration (2.4)].

5.3 Neonatal Opioid Withdrawal Syndrome

Prolonged use of Morphine Sulfate Injection during pregnancy can result in withdrawal in the neonate. Neonatal opioid withdrawal syndrome, unlike opioid withdrawal syndrome in adults, may be life-threatening if not recognized and treated, and requires management according to protocols developed by neonatology experts. Observe newborns for signs of neonatal opioid withdrawal syndrome and manage accordingly. Advise pregnant women using opioids for a prolonged period of the risk of neonatal opioid withdrawal syndrome and ensure that appropriate treatment will be available [see Use in Specific Populations (8.1)].

5.4 Risks from Concomitant Use with Benzodiazepines or Other CNS Depressants

Profound sedation, respiratory depression, coma, and death may result from the concomitant use of Morphine Sulfate Injection with benzodiazepines or other CNS depressants (e.g., non-benzodiazepine sedatives/hypnotics, anxiolytics, tranquilizers, muscle relaxants, general anesthetics, antipsychotics, other opioids, alcohol). Because of these risks, reserve concomitant prescribing of these drugs for use in patients for whom alternative treatment options are inadequate.

Observational studies have demonstrated that concomitant use of opioid analgesics and benzodiazepines increases the risk of drug-related mortality compared to use of opioid analgesics alone. Because of similar pharmacological properties, it is reasonable to expect similar risk with the concomitant use of other CNS depressant drugs with opioid analgesics [see Drug Interactions (7)].

If the decision is made to prescribe a benzodiazepine or other CNS depressant concomitantly with an opioid analgesic, prescribe the lowest effective dosages and minimum durations of concomitant use. In patients already receiving an opioid analgesic, prescribe a lower initial dose of the benzodiazepine or other CNS depressant than indicated in the absence of an opioid, and titrate based on clinical response. If an opioid analgesic is initiated in a patient already taking a benzodiazepine or other CNS depressant, prescribe a lower initial dose of the opioid analgesic, and titrate based on clinical response. Follow patients closely for signs and symptoms of respiratory depression and sedation.

Advise both patients and caregivers about the risks of respiratory depression and sedation when Morphine Sulfate Injection is used with benzodiazepines or other CNS depressants (including alcohol and illicit drugs). Advise patients not to drive or operate heavy machinery until the effects of concomitant use of the benzodiazepine or other CNS depressant have been determined. Screen patients for risk of substance use disorders, including opioid abuse and misuse, and warn them of the risk for overdose and death associated with the use of additional CNS depressants including alcohol and illicit drugs [see Drug Interactions (7)].

5.5 Cardiovascular Instability

While low doses of intravenously administered morphine have little effect on cardiovascular stability, high doses are excitatory, resulting from sympathetic hyperactivity and increase in circulatory catecholamines. Have Naloxone Injection and resuscitative equipment immediately available for use in case of life-threatening or intolerable side effects and whenever morphine therapy is being initiated.

5.6 Life-Threatening Respiratory Depression in Patients with Chronic Pulmonary Disease or in Elderly, Cachectic, or Debilitated Patients

The use of Morphine Sulfate Injection in patients with acute or severe bronchial asthma in an unmonitored setting or in the absence of resuscitative equipment is contraindicated.

Patients with Chronic Pulmonary Disease: Morphine Sulfate Injection-treated patients with significant chronic obstructive pulmonary disease or cor pulmonale, and those with a substantially decreased respiratory reserve, hypoxia, hypercapnia, or pre-existing respiratory depression are at increased risk of decreased respiratory drive including apnea, even at recommended dosages of Morphine Sulfate Injection [see Warnings and Precautions (5.2)]

Elderly, Cachectic, or Debilitated Patients: Life-threatening respiratory depression is more likely to occur in elderly, cachectic, or debilitated patients because they may have altered pharmacokinetics or altered clearance compared to younger, healthier patients [see Warnings and Precautions (5.2)].

Monitor such patients closely, particularly when initiating and titrating Morphine Sulfate Injection and when Morphine Sulfate Injection is given concomitantly with other drugs that depress respiration [see Warnings and Precautions (5.2)]. Alternatively, consider the use of non-opioid analgesics in these patients.

5.7 Interactions with Monoamine Oxidase Inhibitors

Monoamine oxidase inhibitors (MAOIs) may potentiate the effects of morphine, including respiratory depression, coma, and confusion. Morphine Sulfate Injection should not be used in patients taking MAOIs or within 14 days of stopping such treatment.

5.8 Adrenal Insufficiency

Cases of adrenal insufficiency have been reported with opioid use, more often following greater than one month of use. Presentation of adrenal insufficiency may include non-specific symptoms and signs including nausea, vomiting, anorexia, fatigue, weakness, dizziness, and low blood pressure. If adrenal insufficiency is suspected, confirm the diagnosis with diagnostic testing as soon as possible. If adrenal insufficiency is diagnosed, treat with physiologic replacement doses of corticosteroids. Wean the patient off of the opioid to allow adrenal function to recover and continue corticosteroid treatment until adrenal function recovers. Other opioids may be tried as some cases reported use of a different opioid without recurrence of adrenal insufficiency. The information available does not identify any particular opioids as being more likely to be associated with adrenal insufficiency.

5.9 Severe Hypotension

Morphine Sulfate Injection may cause severe hypotension including orthostatic hypotension and syncope in ambulatory patients. There is increased risk in patients whose ability to maintain blood pressure has already been compromised by a reduced blood volume or concurrent administration of certain CNS depressant drugs (e.g., phenothiazines or general anesthetics) [see Drug Interactions (7)]. Monitor these patients for signs of hypotension after initiating or titrating the dosage of Morphine Sulfate Injection. In patients with circulatory shock, Morphine Sulfate Injection may cause vasodilation that can further reduce cardiac output and blood pressure. Avoid the use of Morphine Sulfate Injection in patients with circulatory shock.

5.10 Risks of Use in Patients with Increased Intracranial Pressure, Brain Tumors, Head Injury, or Impaired Consciousness

In patients who may be susceptible to the intracranial effects of CO2 retention (e.g., those with evidence of increased intracranial pressure or brain tumors), Morphine Sulfate Injection may reduce respiratory drive, and the resultant CO2 retention can further increase intracranial pressure. Monitor such patients for signs of sedation and respiratory depression, particularly when initiating therapy with Morphine Sulfate Injection.

Opioids may also obscure the clinical course in a patient with a head injury. Avoid the use of Morphine Sulfate Injection in patients with impaired consciousness or coma.

5.11 Risks of Use in Patients with Gastrointestinal Conditions

Morphine Sulfate Injection is contraindicated in patients with known or suspected gastrointestinal obstruction, including paralytic ileus.

The morphine in Morphine Sulfate Injection may cause spasm of the sphincter of Oddi. Opioids may cause increases in serum amylase. Monitor patients with biliary tract disease, including acute pancreatitis for worsening symptoms.

5.12 Increased Risk of Seizures in Patients with Seizure Disorders

The morphine in Morphine Sulfate Injection, may increase the frequency of seizures in patients with seizure disorders, and may increase the risk of seizures occurring in other clinical settings associated with seizures. Monitor patients with a history of seizure disorders for worsened seizure control during Morphine Sulfate Injection therapy.

5.13 Withdrawal

Avoid the use of mixed agonist/antagonist (e.g, pentazocine, nalbuphine, and butorphanol) or partial agonist (e.g., buprenorphine) analgesics in patients who are receiving a full opioid agonist analgesic, including Morphine Sulfate Injection. In these patients, mixed agonist/antagonist and partial agonist analgesics may reduce the analgesic effect and/or precipitate withdrawal symptoms.

When discontinuing Morphine Sulfate Injection in a physically-dependent patient, gradually taper the dosage [see Dosage and Administration (2.4)]. Do not abruptly discontinue Morphine Sulfate Injection in these patients [see Drug Abuse and Dependence (9.3)].

5.14 Central Nervous System Toxicity

Dysphoric reactions may occur after any size dose and toxic psychoses have been reported.

5.15 Exposure, Hypothermia, Immersion and Shock

Caution must be used when injecting any opioid intramuscularly into chilled areas or in patients with hypotension or shock, since impaired perfusion may prevent complete absorption; if repeated injections are administered, an excessive amount may be suddenly absorbed if normal circulation is re-established.

5.16 Risks of Driving and Operating Machinery

Morphine Sulfate Injection may impair the mental or physical abilities needed to perform potentially hazardous activities such as driving a car or operating machinery. Warn patients not to drive or operate dangerous machinery unless they are tolerant to the effects of Morphine Sulfate Injection and know how they will react to the medication.

6 ADVERSE REACTIONS

The following serious adverse reactions are described, or described in greater detail, in other sections:

- Addiction, Abuse, and Misuse [see Warnings and Precautions (5.1)]
- Life-Threatening Respiratory Depression [see Warnings and Precautions (5.2)]
- Neonatal Opioid Withdrawal Syndrome [see Warnings and Precautions (5.3)]
- Interactions with Benzodiazepine or Other CNS Depressants [see Warnings and Precautions (5.4)]
- Cardiovascular Instability [see Warnings and Precautions (5.5)]
- Adrenal Insufficiency [see Warnings and Precautions (5.8)]
- Severe Hypotension [see Warnings and Precautions (5.9)]
- Gastrointestinal Adverse Reactions [see Warnings and Precautions (5.11)]
- Seizures [see Warnings and Precautions (5.12)]
- Withdrawal [see Warnings and Precautions (5.13)]

The following adverse reactions associated with the use of morphine were identified in clinical studies or postmarketing reports. Because some of these reactions were reported voluntarily from a population of uncertain size, it is not always possible to reliably estimate their frequency or establish a causal relationship to drug exposure.

Serious adverse reactions associated with Morphine Sulfate Injection included, respiratory depression, apnea, and to a lesser degree, circulatory depression, respiratory arrest, shock and cardiac arrest. Rarely, anaphylactoid reactions have been reported when morphine or other phenanthrene alkaloids of opium are administered intravenously.

The most frequently observed adverse reactions included sedation, lightheadedness, dizziness, nausea, vomiting, constipation and diaphoresis.

Other possible adverse reactions include:

Central Nervous System – Euphoria, dysphoria, weakness, headache, agitation, tremor, uncoordinated muscle movements, visual disturbances, transient hallucinations and disorientation.

Gastrointestinal – Constipation, biliary tract spasm.

Cardiovascular – Tachycardia, bradycardia, palpitation, faintness, syncope and orthostatic hypotension.

Genitourinary – Oliguria and urinary retention; an antidiuretic effect has been reported.

Allergic – Pruritus, urticaria and skin rashes. Anaphylactoid reactions have been reported following intravenous administration.

Other – Opioid-induced histamine release may be responsible for the flushing of the face, diaphoresis and pruritus often seen with these drugs. Wheals and urticaria at the site of injection are probably related to histamine release. Local tissue irritation, pain and induration have been reported following repeated subcutaneous injection. Androgen deficiency: Cases of androgen deficiency have occurred with chronic use of opioids [see Clinical Pharmacology (12.2)].

Anaphylaxis: Anaphylaxis has been reported with ingredients contained in Morphine Sulfate Injection.

Serotonin syndrome: Cases of serotonin syndrome, a potentially life-threatening condition, have been reported during concomitant use of opioids with serotonergic drugs.

Adrenal insufficiency: Cases of adrenal insufficiency have been reported with opioid use, more often following greater than one month of use.

7 DRUG INTERACTIONS

Table 1 includes clinically significant drug interactions with Morphine Sulfate Injection.

Table 1: Clinically Significant Drug Interactions with Morphine Sulfate Injection
Benzodiazepines and Other Central Nervous System (CNS) Depressants
Clinical Impact: | Due to additive pharmacologic effect, the concomitant use of benzodiazepines or other CNS depressants, including alcohol, can increase the risk of hypotension, respiratory depression, profound sedation, coma, and death.
Intervention: | Reserve concomitant prescribing of these drugs for use in patients for whom alternative treatment options are inadequate. Limit dosages and durations to the minimum required. Follow patients closely for signs of respiratory depression and sedation [see Warnings and Precautions (5.4)].
Examples: | Benzodiazepines and other sedatives/hypnotics, anxiolytics, tranquilizers, muscle relaxants, general anesthetics, antipsychotics, other opioids, alcohol.
Serotonergic Drugs
Clinical Impact: | The concomitant use of opioids with other drugs that affect the serotonergic neurotransmitter system has resulted in serotonin syndrome.
Intervention: | If concomitant use is warranted, carefully observe the patient, particularly during treatment initiation and dose adjustment. Discontinue Morphine Sulfate Injection if serotonin syndrome is suspected.
Examples: | Selective serotonin reuptake inhibitors (SSRIs), serotonin and norepinephrine reuptake inhibitors (SNRIs), tricyclic antidepressants (TCAs), triptans, 5-HT3 receptor antagonists, drugs that affect the serotonin neurotransmitter system (e.g., mirtazapine, trazodone, tramadol), monoamine oxidase (MAO) inhibitors (those intended to treat psychiatric disorders and also others, such as linezolid and intravenous methylene blue).
Monoamine Oxidase Inhibitors (MAOIs)
Clinical Impact: | MAOI interactions with opioids may manifest as serotonin syndrome or opioid toxicity (e.g., respiratory depression, coma) [see Warnings and Precautions (5.7)].
Intervention: | Do not use Morphine Sulfate Injection in patients taking MAOIs or within 14 days of stopping such treatment. If urgent use of an opioid is necessary, use test doses and frequent titration of small doses of other opioids (such as oxycodone, hydrocodone, oxymorphone, or buprenorphine) to treat pain while closely monitoring blood pressure and signs and symptoms of CNS and respiratory depression.
Examples: | phenelzine, tranylcypromine, linezolid
Mixed Agonist/Antagonist and Partial Agonist Opioid Analgesics
Clinical Impact: | May reduce the analgesic effect of Morphine Sulfate Injection and/or precipitate withdrawal symptoms.
Intervention: | Avoid concomitant use.
Examples: | butorphanol, nalbuphine, pentazocine, buprenorphine.
Muscle Relaxants
Clinical Impact: | Morphine may enhance the neuromuscular blocking action of skeletal muscle relaxants and produce an increased degree of respiratory depression.
Intervention: | Monitor patients for signs of respiratory depression that may be greater than otherwise expected and decrease the dosage of Morphine Sulfate Injection and/or the muscle relaxant as necessary.
Cimetidine
Clinical Impact: | The concomitant administration of morphine sulfate and cimetidine has been reported to precipitate apnea, confusion and muscle twitching in an isolated report.
Intervention: | Monitor patients for increased respiratory and CNS depression when receiving cimetidine concomitantly with Morphine Sulfate Injection.
Diuretics
Clinical Impact: | Opioids can reduce the efficacy of diuretics by inducing the release of antidiuretic hormone.
Intervention: | Monitor patients for signs of diminished diuresis and/or effects on blood pressure and increase the dosage of the diuretic as needed.
Anticholinergic Drugs
Clinical Impact: | The concomitant use of anticholinergic drugs may increase risk of urinary retention and/or severe constipation, which may lead to paralytic ileus.
Intervention: | Monitor patients for signs of urinary retention or reduced gastric motility when Morphine Sulfate Injection is used concomitantly with anticholinergic drugs.
Oral P2Y12 Inhibitors
Clinical Impact: | The co-administration of oral P2Y12 inhibitors and intravenous morphine sulfate can decrease the absorption and peak concentration of oral P2Y12 inhibitors and delay the antiplatelet effect.
Intervention: | Consider the use of a parenteral antiplatelet agent in the setting of acute coronary syndrome requiring coadministration of intravenous morphine sulfate.
Examples: | clopidogrel, prasugrel, ticagrelor

8 USE IN SPECIFIC POPULATIONS

8.1 Pregnancy

Risk Summary

Prolonged use of opioid analgesics during pregnancy can cause neonatal opioid withdrawal syndrome [see Warnings and Precautions (5.3)]. There are no available data with Morphine Sulfate Injection in pregnant women to inform a drug-associated risk for major birth defects and miscarriage. Published studies with morphine use during pregnancy have not reported a clear association with morphine and major birth defects [see Human Data]. In published animal reproduction studies, morphine administered subcutaneously during the early gestational period produced neural tube defects (i.e., exencephaly and cranioschisis) at 5 and 16 times the human daily dose of 60 mg based on body surface area (HDD) in hamsters and mice, respectively, lower fetal body weight and increased incidence of abortion at 0.4 times the HDD in the rabbit, growth retardation at 6 times the HDD in the rat, and axial skeletal fusion and cryptorchidism at 16 times the HDD in the mouse. Administration of morphine sulfate to pregnant rats during organogenesis and through lactation resulted in cyanosis, hypothermia, decreased brain weights, pup mortality, decreased pup body weights, and adverse effects on reproductive tissues at 3-4 times the HDD; and long-term neurochemical changes in the brain of offspring which correlate with altered behavioral responses that persist through adulthood at exposures comparable to and less than the HDD [see Animal Data]. Based on animal data, advise pregnant women of the potential risk to a fetus.

All pregnancies have a background risk of birth defect, loss, or other adverse outcomes. In the U.S. general population, the estimated background risk of major birth defects and miscarriage in clinically recognized pregnancies is 2-4% and 15-20%, respectively.

Clinical Considerations

Fetal/Neonatal Adverse Reactions

Prolonged use of opioid analgesics during pregnancy for medical or nonmedical purposes can result in physical dependence in the neonate and neonatal opioid withdrawal syndrome shortly after birth. Neonatal opioid withdrawal syndrome presents as irritability, hyperactivity and abnormal sleep pattern, high pitched cry, tremor, vomiting, diarrhea, and failure to gain weight. The onset, duration, and severity of neonatal opioid withdrawal syndrome vary based on the specific opioid used, duration of use, timing and amount of last maternal use, and rate of elimination of the drug by the newborn. Observe newborns for symptoms of neonatal opioid withdrawal syndrome and manage accordingly [see Warnings and Precautions (5.3)].

Labor or Delivery

Opioids cross the placenta and may produce respiratory depression and psycho-physiologic effects in neonates. An opioid antagonist, such as naloxone, must be available for reversal of opioid-induced respiratory depression in the neonate. Morphine Sulfate Injection is not recommended for use in pregnant women during or immediately prior to labor, when other analgesic techniques are more appropriate. Opioid analgesics, including Morphine Sulfate Injection, can prolong labor through actions which temporarily reduce the strength, duration, and frequency of uterine contractions. However, this effect is not consistent and may be offset by an increased rate of cervical dilation, which tends to shorten labor. Monitor neonates exposed to opioid analgesics during labor for signs of excess sedation and respiratory depression.

Data

Human Data

The results from a population-based prospective cohort, including 70 women exposed to morphine during the first trimester of pregnancy and 448 women exposed to morphine at any time during pregnancy, indicate no increased risk for congenital malformations. However, these studies cannot definitely establish the absence of any risk because of methodological limitations, including small sample size and non-randomized study design.

Animal Data

Formal reproductive and developmental toxicology studies for morphine have not been conducted. Exposure margins for the following published study reports are based on human daily dose of 60 mg morphine using a body surface area comparison (HDD).

Neural tube defects (exencephaly and cranioschisis) were noted following subcutaneous administration of morphine sulfate (35-322 mg/kg) on Gestation Day 8 to pregnant hamsters (4.7 to 43.5 times the HDD). A no adverse effect level was not defined in this study and the findings cannot be clearly attributed to maternal toxicity. Neural tube defects (exencephaly), axial skeletal fusions, and cryptorchidism were reported following a single subcutaneous (SC) injection of morphine sulfate to pregnant mice (100-500 mg/kg) on Gestation Day 8 or 9 at 200 mg/kg or greater (16 times the HDD) and fetal resorption at 400 mg/kg or higher (32 times the HDD). No adverse effects were noted following 100 mg/kg morphine in this model (8 times the HDD). In one study, following continuous subcutaneous infusion of doses greater than or equal to 2.72 mg/kg to mice (0.2 times the HDD), exencephaly, hydronephrosis, intestinal hemorrhage, split supraoccipital, malformed sternebrae, and malformed xiphoid were noted. The effects were reduced with increasing daily dose; possibly due to rapid induction of tolerance under these infusion conditions. The clinical significance of this report is not clear.

Decreased fetal weights were observed in pregnant rats treated with 20 mg/kg/day morphine sulfate (3.2 times the HDD) from Gestation Day 7 to 9. There was no evidence of malformations despite maternal toxicity (10% mortality). In a second rat study, decreased fetal weight and increased incidences of growth retardation were noted at 35 mg/kg/day (5.7 times the HDD) and there was a reduced number of fetuses at 70 mg/kg/day (11.4 times the HDD) when pregnant rats were treated with 10, 35, or 70 mg/kg/day morphine sulfate via continuous infusion from Gestation Day 5 to 20. There was no evidence of fetal malformations or maternal toxicity.

An increased incidence of abortion was noted in a study in which pregnant rabbits were treated with 2.5 (0.8 times the HDD) to 10 mg/kg morphine sulfate via subcutaneous injection from Gestation Day 6 to 10. In a second study, decreased fetal body weights were reported following treatment of pregnant rabbits with increasing doses of morphine (10-50 mg/kg/day) during the pre-mating period and 50 mg/kg/day (16 times the HDD) throughout the gestation period. No overt malformations were reported in either publication; although only limited endpoints were evaluated.

In published studies in rats, exposure to morphine during gestation and/or lactation periods is associated with: decreased pup viability at 12.5 mg/kg/day or greater (2 times the HDD); decreased pup body weights at 15 mg/kg/day or greater (2.4 times the HDD); decreased litter size, decreased absolute brain and cerebellar weights, cyanosis, and hypothermia at 20 mg/kg/day (3.2 times the HDD); alteration of behavioral responses (play, social-interaction) at 1 mg/kg/day or greater (0.2 times the HDD); alteration of maternal behaviors (e.g., decreased nursing and pup retrievals) in mice at 1 mg/kg or higher (0.08 times the HDD) and rats at 1.5 mg/kg/day or higher (0.2 times the HDD); and a host of behavioral abnormalities in the offspring of rats, including altered responsiveness to opioids at 4 mg/kg/day (0.7 times the HDD) or greater.

Fetal and/or postnatal exposure to morphine in mice and rats has been shown to result in morphological changes in fetal and neonatal brain and neuronal cell loss, alteration of a number of neurotransmitter and neuromodulator systems, including opioid and non-opioid systems, and impairment in various learning and memory tests that appear to persist into adulthood. These studies were conducted with morphine treatment usually in the range of 4 to 20 mg/kg/day (0.7 to 3.2 times the HDD).

Additionally, delayed sexual maturation and decreased sexual behaviors in female offspring at 20 mg/kg/day (3.2 times the HDD), and decreased plasma and testicular levels of luteinizing hormone and testosterone, decreased testes weights, seminiferous tubule shrinkage, germinal cell aplasia, and decreased spermatogenesis in male offspring were also observed at 20 mg/kg/day (3.2 times the HDD). Decreased litter size and viability were observed in the offspring of male rats that were intraperitoneally administered morphine sulfate for 1 day prior to mating at 25 mg/kg/day (4.1 times the HDD) and mated to untreated females. Decreased viability and body weight and/or movement deficits in both first and second generation offspring were reported when male mice were treated for 5 days with escalating doses of 120 to 240 mg/kg/day morphine sulfate (9.7 to 19.5 times the HDD) or when female mice treated with escalating doses of 60 to 240 mg/kg/day (4.9 to 19.5 times the HDD) followed by a 5-day treatment-free recovery period prior to mating. Similar multigenerational findings were also seen in female rats pre-gestationally treated with escalating doses of 10 to 22 mg/kg/day morphine (1.6 to 3.6 times the HDD).

8.2 Lactation

Risk Summary

Morphine is present in breast milk. Published lactation studies report variable concentrations of morphine in breast milk with administration of immediate-release morphine to nursing mothers in the early postpartum period with a milk-to-plasma morphine AUC ratio of 2.5:1 measured in one lactation study. However, there is insufficient information to determine the effects of morphine on the breastfed infant and the effects of morphine on milk production. Lactation studies have not been conducted with Morphine Sulfate Injection and no information is available on the effects of the drug on the breastfed infant or the effects of the drug on milk production.

The developmental and health benefits of breastfeeding should be considered along with the mother's clinical need for Morphine Sulfate Injection and any potential adverse effects on the breastfed infant from Morphine Sulfate Injection or from the underlying maternal condition.

Clinical Considerations

Infants exposed to Morphine Sulfate Injection through breast milk should be monitored for excess sedation and respiratory depression. Withdrawal symptoms can occur in breastfed infants when maternal administration of an opioid analgesic is stopped, or when breast-feeding is stopped.

8.3 Females and Males of Reproductive Potential

Infertility

Chronic use of opioids may cause reduced fertility in females and males of reproductive potential. It is not known whether these effects on fertility are reversible [see Adverse Reactions (6)].

In published animal studies, morphine administration adversely effected fertility and reproductive endpoints in male rats and prolonged estrus cycle in female rats [see Nonclinical Toxicology (13)].

8.4 Pediatric Use

The safety and effectiveness of Morphine Sulfate Injection in pediatric patients below the age of 18 have not been established.

8.5 Geriatric Use

The pharmacodynamic effects of morphine in the elderly are more variable than in the younger population. Older patients will vary widely in the effective initial dose, rate of development of tolerance and the frequency and magnitude of associated adverse effects as the dose is increased.

Elderly patients (aged 65 years or older) may have increased sensitivity to morphine. In general, use caution when selecting a dosage for an elderly patient, usually starting at the low end of the dosing range, reflecting the greater frequency of decreased hepatic, renal, or cardiac function and of concomitant disease or other drug therapy. Respiratory depression is the chief risk for elderly patients treated with opioids, and has occurred after large initial doses were administered to patients who were not opioid-tolerant or when opioids were co-administered with other agents that depress respiration. Titrate the dosage of Morphine Sulfate Injection slowly in geriatric patients and monitor for signs of central nervous system and respiratory depression [see Warnings and Precautions (5.6)].

Morphine is known to be substantially excreted by the kidney, and the risk of adverse reactions to this drug may be greater in patients with impaired renal function. Because elderly patients are more likely to have decreased renal function, care should be taken in dose selection, and it may be useful to monitor renal function.

8.6 Hepatic Impairment

Morphine sulfate pharmacokinetics have been reported to be significantly altered in patients with cirrhosis. Start these patients with a lower than normal dosage of Morphine Sulfate Injection and titrate slowly while monitoring for signs of respiratory depression, sedation, and hypotension [see Clinical Pharmacology (12.3)].

8.7 Renal Impairment

Morphine sulfate pharmacokinetics are altered in patients with renal failure. Start these patients with a lower than normal dosage of Morphine Sulfate Injection and titrate slowly while monitoring for signs of respiratory depression, sedation, and hypotension [see Clinical Pharmacology (12.3)].

9 DRUG ABUSE AND DEPENDENCE

9.1 Controlled Substance

Morphine Sulfate Injection contains morphine, a Schedule II controlled substance.

9.2 Abuse

Morphine Sulfate Injection contains morphine, a substance with a high potential for abuse similar to other opioids including fentanyl, hydrocodone, hydromorphone, methadone, oxycodone, oxymorphone, and tapentadol. Morphine Sulfate Injection can be abused and is subject to misuse, addiction, and criminal diversion [see Warnings and Precautions (5.1)].

All patients treated with opioids require careful monitoring for signs of abuse and addiction, because use of opioid analgesic products carries the risk of addiction even under appropriate medical use.

Prescription drug abuse is the intentional non-therapeutic use of a prescription drug, even once, for its rewarding psychological or physiological effects.

Drug addiction is a cluster of behavioral, cognitive, and physiological phenomena that develop after repeated substance use and includes: a strong desire to take the drug, difficulties in controlling its use, persisting in its use despite harmful consequences, a higher priority given to drug use than to other activities and obligations, increased tolerance, and sometimes a physical withdrawal.

“Drug-seeking” behavior is very common in persons with substance use disorders. Drug-seeking tactics include emergency calls or visits near the end of office hours, refusal to undergo appropriate examination, testing, or referral, repeated “loss” of prescriptions, tampering with prescriptions, and reluctance to provide prior medical records or contact information for other treating healthcare provider(s). “Doctor shopping” (visiting multiple prescribers to obtain additional prescriptions) is common among drug abusers and people suffering from untreated addiction. Preoccupation with achieving adequate pain relief can be appropriate behavior in a patient with poor pain control.

Abuse and addiction are separate and distinct from physical dependence and tolerance. Health care providers should be aware that addiction may not be accompanied by concurrent tolerance and symptoms of physical dependence in all addicts. In addition, abuse of opioids can occur in the absence of true addiction.

Morphine Sulfate Injection, like other opioids, can be diverted for non-medical use into illicit channels of distribution. Careful record-keeping of prescribing information, including quantity, frequency, and renewal requests, as required by state and federal law, is strongly advised.

Proper assessment of the patient, proper prescribing practices, periodic re-evaluation of therapy, and proper dispensing and storage are appropriate measures that help to limit abuse of opioid drugs.

9.3 Dependence

Both tolerance and physical dependence can develop during chronic opioid therapy. Tolerance is the need for increasing doses of opioids to maintain a defined effect such as analgesia (in the absence of disease progression or other external factors). Tolerance may occur to both the desired and undesired effects of drugs, and may develop at different rates for different effects.

Physical dependence results in withdrawal symptoms after abrupt discontinuation or a significant dosage reduction of a drug. Withdrawal also may be precipitated through the administration of drugs with opioid antagonist activity (e.g., naloxone, nalmefene), mixed agonist/antagonist analgesics (e.g., pentazocine, butorphanol, nalbuphine), or partial agonists (e.g., buprenorphine). Physical dependence may not occur to a clinically significant degree until after several days to weeks of continued opioid usage.

Morphine Sulfate Injection should not be abruptly discontinued in a physically-dependent patient [see Dosage and Administration (2.4)]. If Morphine Sulfate Injection is abruptly discontinued in a physically-dependent patient, a withdrawal syndrome may occur. Some or all of the following can characterize this syndrome: restlessness, lacrimation, rhinorrhea, yawning, perspiration, chills, myalgia, and mydriasis. Other signs and symptoms also may develop, including irritability, anxiety, backache, joint pain, weakness, abdominal cramps, insomnia, nausea, anorexia, vomiting, diarrhea, or increased blood pressure, respiratory rate, or heart rate.

Infants born to mothers physically dependent on opioids will also be physically dependent and may exhibit respiratory difficulties and withdrawal signs [see Use in Specific Populations (8.1)].

10 OVERDOSAGE

Clinical Presentation

Acute overdose with Morphine Sulfate Injection can be manifested by respiratory depression, somnolence progressing to stupor or coma, skeletal muscle flaccidity, cold and clammy skin, constricted pupils, and, in some cases, pulmonary edema, bradycardia, hypotension, partial or complete airway obstruction, snoring, and death. Marked mydriasis rather than miosis may be seen with hypoxia in overdose [see Clinical Pharmacology (12.2)].

Treatment of Overdose

In case of overdose, priorities are the reestablishment of a patent and protected airway and institution of assisted or controlled ventilation, if needed. Employ other supportive measures (including oxygen and vasopressors) in the management of circulatory shock and pulmonary edema as indicated. Cardiac arrest or arrhythmias will require advanced life-support techniques.

The opioid antagonists, naloxone or nalmefene, are specific antidotes to respiratory depression resulting from opioid overdose. For clinically significant respiratory or circulatory depression secondary to morphine overdose, administer an opioid antagonist. Opioid antagonists should not be administered in the absence of clinically significant respiratory or circulatory depression secondary to morphine overdose.

Because the duration of opioid reversal is expected to be less than the duration of action of morphine in Morphine Sulfate Injection, carefully monitor the patient until spontaneous respiration is reliably reestablished. If the response to an opioid antagonist is suboptimal or only brief in nature, administer additional antagonist as directed by the product's prescribing information.

In an individual physically dependent on opioids, administration of the recommended usual dosage of the antagonist will precipitate an acute withdrawal syndrome. The severity of the withdrawal symptoms experienced will depend on the degree of physical dependence and the dose of the antagonist administered. If a decision is made to treat serious respiratory depression in the physically dependent patient, administration of the antagonist should be begun with care and by titration with smaller than usual doses of the antagonist.

11 DESCRIPTION

Morphine sulfate is an opioid agonist. Morphine Sulfate Injection USP is available as a sterile, nonpyrogenic solution of morphine sulfate, free of antioxidants and preservatives in single-dose prefilled syringes for intravenous and intramuscular administration.

The chemical name for Morphine sulfate is 7,8-Didehydro-4,5-epoxy-17-methyl-(5α,6α)-morphinan-3,6 α -diol sulfate (2: 1) (salt), pentahydrate. The molecular weight is 758.83. Its molecular formula is (C17H19NO3)2 • H2SO4 • 5H2O and it has the following chemical structure.

Morphine sulfate is a fine white powder. When exposed to air it gradually loses water of hydration, and darkens on prolonged exposure to light. It is soluble in water and ethanol at room temperature. Each 1 mL single-dose pre-filled syringe contains 2 mg (equivalent to 1.75 mg Morphine), 4 mg (equivalent to 3.50 mg Morphine), 5 mg (equivalent to 4.37 mg Morphine), 8 mg (equivalent to 6.99 mg Morphine) or 10 mg (equivalent to 8.73 mg Morphine) of Morphine Sulfate USP in 1 mL total volume of water for injection solution with inactive ingredients. The inactive ingredients in Morphine Sulfate Injection, USP include:

- For the 2 mg/mL and 4 mg/mL products: 8.4 mg sodium chloride, 2.3 mg of sodium citrate, 0.74 mg of citric acid, 0.111 mg of edetate disodium, 0.053 mg of calcium chloride and water for injection.
- For the 5 mg/mL, 8 mg/mL and 10 mg/mL products: 7.5 mg sodium chloride, 3.45 mg of sodium citrate, 1.11 mg of citric acid, 0.111 mg of edetate disodium, 0.053 mg of calcium chloride and water for injection.

12 CLINICAL PHARMACOLOGY

12.1 Mechanism of Action

Morphine is a full opioid agonist and is relatively selective for the mu-opioid receptor, although it can bind to other opioid receptors at higher doses. The principal therapeutic action of morphine is analgesia. Like all full opioid agonists, there is no ceiling effect for analgesia with morphine. Clinically, dosage is titrated to provide adequate analgesia and may be limited by adverse reactions, including respiratory and CNS depression.

The precise mechanism of the analgesic action is unknown. However, specific CNS opioid receptors for endogenous compounds with opioid-like activity have been identified throughout the brain and spinal cord and are thought to play a role in the analgesic effects of this drug.

12.2 Pharmacodynamics

Effects on the Central Nervous System

Morphine produces respiratory depression by direct action on brain stem respiratory centers. The respiratory depression involves a reduction in the responsiveness of the brain stem respiratory centers to both increases in carbon dioxide tension and electrical stimulation.

Morphine causes miosis, even in total darkness. Pinpoint pupils are a sign of opioid overdose but are not pathognomonic (e.g., pontine lesions of hemorrhagic or ischemic origins may produce similar findings). Marked mydriasis rather than miosis may be seen due to hypoxia in overdose situations.

Effects on the Gastrointestinal Tract and Other Smooth Muscle

Morphine causes a reduction in motility associated with an increase in smooth muscle tone in the antrum of the stomach and duodenum. Digestion of food in the small intestine is delayed and propulsive contractions are decreased. Propulsive peristaltic waves in the colon are decreased, while tone may be increased to the point of spasm, resulting in constipation. Other opioid-induced effects may include a reduction in biliary and pancreatic secretions, spasm of sphincter of Oddi, and transient elevations in serum amylase. Morphine may also cause spasm of the sphincter of the urinary bladder.

Effects on the Cardiovascular System

In therapeutic doses, morphine does not usually exert major effects on the cardiovascular system. Morphine produces peripheral vasodilation, which may result in orthostatic hypotension or syncope. Manifestations of histamine release and/or peripheral vasodilation may include pruritus, flushing, red eyes, sweating and/or orthostatic hypotension.

Effects on the Endocrine System

Opioids inhibit the secretion of adrenocorticotropic hormone (ACTH), cortisol, and luteinizing hormone (LH) in humans. [see Adverse Reactions (6)]. They also stimulate prolactin, growth hormone (GH) secretion, and pancreatic secretion of insulin and glucagon.

Chronic use of opioids may influence the hypothalamic-pituitary-gonadal axis, leading to androgen deficiency that may manifest as low libido, impotence, erectile dysfunction, amenorrhea, or infertility. The causal role of opioids in the clinical syndrome of hypogonadism is unknown because the various medical, physical, lifestyle, and psychological stressors that may influence gonadal hormone levels have not been adequately controlled for in studies conducted to date [see Adverse Reactions (6)].

Effects on the Immune System

Opioids have been shown to have a variety of effects on components of the immune system in in vitro and animal models. The clinical significance of these findings is unknown. Overall, the effects of opioids appear to be modestly immunosuppressive.

Concentration–Efficacy Relationships

The minimum effective analgesic concentration will vary widely among patients, especially among patients who have been previously treated with potent agonist opioids. The minimum effective analgesic concentration of morphine for any individual patient may increase over time due to an increase in pain, the development of a new pain syndrome, and/or the development of analgesic tolerance. [see Dosage and Administration (2.1, 2.3)]

Onset of analgesia occurs with 5-20 minutes following intramuscular administration of morphine, rising to peak analgesia sixty minutes after a single intramuscular injection. The duration of analgesia after a single injection is usually three to four hours.

Concentration–Adverse Reaction Relationships

There is a relationship between increasing morphine plasma concentration and increasing frequency of dose-related opioid adverse reactions such as nausea, vomiting, CNS effects, and respiratory depression. In opioid-tolerant patients, the situation may be altered by the development of tolerance to opioid-related adverse reactions [see Dosage and Administration (2.1, 2.2)].

12.3 Pharmacokinetics

Absorption: Average peak morphine plasma levels of 67.4 ± 22.5 ng/mL were noted around 5 to 30 minutes following intramuscular injection of 10 mg morphine sulfate from a prefilled syringe.

Distribution: Morphine has an apparent volume of distribution ranging from 1.0 to 4.7 L/kg after intravenous dosage. Protein binding is low, about 36%, and muscle tissue binding is reported as 54%. A blood-brain barrier exists, and when morphine is introduced outside of the CNS (e.g., intravenously), plasma concentrations of morphine remain higher than the corresponding CSF morphine sulfate levels.

Elimination:

Morphine has a total plasma clearance which ranges from 0.9 to 1.2 L/kg/h (liters/kilogram/hour) in postoperative patients, but shows considerable interindividual variation. Terminal half-life is commonly reported to vary from 1.5 to 4.5 hours, although the longer half-lives were obtained when morphine levels were monitored over protracted periods with very sensitive radioimmunoassay methods. The accepted elimination half-life in normal subjects is 1.5 to 2 hours.

Metabolism
The major pathway of clearance is hepatic glucuronidation to morphine -3-glucuronide, which is pharmacologically inactive.
Excretion
The major excretion path of the conjugate is through the kidneys, with about 10% in the feces. Morphine is also eliminated by the kidneys, 2 to 12% being excreted unchanged in the urine.

Specific Populations

Sex

While evidence of greater post-operative Morphine Sulfate Injection consumption in men compared to women is present in the literature, clinically significant differences in analgesic outcomes and pharmacokinetic parameters have not been consistently demonstrated. Some studies have shown an increased sensitivity to the adverse effects of Morphine Sulfate Injection USP, including respiratory depression, in women compared to men.

Hepatic Impairment

Morphine pharmacokinetics are altered in patients with cirrhosis. Clearance was found to decrease with a corresponding increase in half-life. The M3G and M6G to morphine sulfate AUC ratio is also decreased in these subjects, indicating diminished metabolic activity. Adequate studies of the pharmacokinetics of morphine in patients with severe hepatic impairment have not been conducted.

Renal Impairment

Morphine pharmacokinetics are altered in patients with renal failure. AUC is increased and clearance is decreased and the metabolites, M3G and M6G, may accumulate to much higher plasma levels in patients with renal failure as compared to patients with normal renal function. Adequate studies of the pharmacokinetics of morphine in patients with severe renal impairment have not been conducted.

13 NONCLINICAL TOXICOLOGY

13.1 Carcinogenesis, Mutagenesis, Impairment of Fertility

Carcinogenesis

Long-term studies in animals to evaluate the carcinogenic potential of morphine have not been conducted.

Mutagenesis

No formal studies to assess the mutagenic potential of morphine have been conducted. In the published literature, morphine was found to be mutagenic in vitro increasing DNA fragmentation in human T-cells. Morphine was also reported to be mutagenic in the in vivo mouse micronucleus assay and positive for the induction of chromosomal aberrations in mouse spermatids and murine lymphocytes. Mechanistic studies suggest that the in vivo clastogenic effects reported with morphine in mice may be related to increases in glucocorticoid levels produced by morphine in these species. In contrast to the above positive findings, in vitro studies in the literature have also shown that morphine did not induce chromosomal aberrations in human leukocytes or translocations or lethal mutations in Drosophila.

Impairment of Fertility

No formal nonclinical studies to assess the potential of morphine to impair fertility have been conducted.

Several nonclinical studies from the literature have demonstrated adverse effects on male fertility in the rat from exposure to morphine. One study in which male rats were administered morphine sulfate subcutaneously prior to mating (up to 30 mg/kg twice daily) and during mating (20 mg/kg twice daily) with untreated females, a number of adverse reproductive effects including reduction in total pregnancies and higher incidence of pseudopregnancies at 20 mg/kg/day (3.2 times the HDD) were reported.

Studies from the literature have also reported changes in hormonal levels in male rats (i.e. testosterone, luteinizing hormone) following treatment with morphine at 10 mg/kg/day or greater (1.6 times the HDD).

Female rats that were administered morphine sulfate intraperitoneally prior to mating exhibited prolonged estrous cycles at 10 mg/kg/day (1.6 times the HDD).

Exposure of adolescent male rats to morphine has been associated with delayed sexual maturation and following mating to untreated females, smaller litters, increased pup mortality, and/or changes in reproductive endocrine status in adult male offspring have been reported (estimated 5 times the plasma levels at the HDD).

16 HOW SUPPLIED/STORAGE AND HANDLING

Morphine Sulfate Injection is available for intravenous (IV) or intramuscular (IM) use as:

Product Code | Unit of Sale | Strength | Each
764412 | NDC 76045-004-12 Unit of 24 | 2 mg/mL | NDC 76045-004-02 1 mL single-dose prefilled syringe
764512 | NDC 76045-005-12 Unit of 24 | 4 mg/mL | NDC 76045-005-02 1 mL single-dose prefilled syringe
764612 | NDC 76045-006-12 Unit of 24 | 5 mg/mL | NDC 76045-006-02 1 mL single-dose prefilled syringe
764710 | NDC 76045-007-10 Unit of 24 | 8 mg/mL | NDC 76045-007-00 1 mL single-dose prefilled syringe
764810 | NDC 76045-008-10 Unit of 24 | 10 mg/mL | NDC 76045-008-00 1 mL single-dose prefilled syringe

Store at 20°C to 25°C (68°F to 77°F) [See USP Controlled Room Temperature.]

PROTECT FROM LIGHT. DO NOT FREEZE.

This product is for single dose only.

17 PATIENT COUNSELING INFORMATION

Serotonin Syndrome

Opioids can cause a rare but potentially life-threatening condition resulting from concomitant administration of serotonergic drugs. Instruct patients to inform their healthcare providers if they are taking, or plan to take serotonergic medications [see Drug Interactions (7)].

Constipation

Advise patients of the potential for severe constipation [see Clinical Pharmacology (12.2)].

INSTRUCTIONS FOR USE

Figure 1: Outer Packaging and Prefilled Syringe

NOTES:

- Do not introduce any other fluid into the syringe at any time.
- Do not dilute for IV push.
- Do not re-sterilize the syringe.
- Do not use this product on a sterile field.
- This product is for single dose only.
1. Inspect the outer packaging (blister pack) to confirm the integrity of the packaging. Do not use if the blister pack or the prefilled syringe has been damaged.
Remove the syringe from the outer packaging. (See Figure 2)
Figure 2
2. Visually inspect the syringe. Parenteral drug products should be inspected visually for particulate matter and discoloration prior to administration, whenever solution and container permit.
Twist off the syringe tip cap. Do not remove the label around the luer lock collar. (See Figure 3)
Figure 3
3. Expel air bubble(s). Adjust the dose (if applicable).
4. Administer the dose ensuring that pressure is maintained on the plunger rod during the entire administration.
5. Discard the used syringe into an appropriate receptacle.

For more information concerning this drug, please call Fresenius Kabi USA, LLC at 1-800-551-7176.

To report SUSPECTED ADVERSE REACTIONS, contact Fresenius Kabi USA, LLC at 1-800-551-7176 or FDA at 1-800-FDA-1088 or www.fda.gov/medwatch.

U.S. Patents 9,072,781; 9,192,608; and 9,731,082

The brand names mentioned in this document are the trademarks of their respective owners.

Lake Zurich, IL 60047

www.fresenius-kabi.com/us

451509F

PACKAGE LABEL

PACKAGE LABEL - PRINCIPAL DISPLAY – Morphine 1 mL Carton Panel
Rx only NDC 76045-004-12
Morphine Sulfate Injection, USP CII
2 mg/mL
For Intramuscular or Intravenous use.

Do NOT place syringe on a Sterile Field.

24 X 1 mL single-dose prefilled syringes

PACKAGE LABEL

PACKAGE LABEL - PRINCIPAL DISPLAY – Morphine 1 mL Blister Pack Label
Rx only NDC 76045-004-02
Morphine Sulfate Injection, USP CII
2 mg/mL
For IM or IV use.

1 mL single-dose prefilled syringe

PACKAGE LABEL

PACKAGE LABEL - PRINCIPAL DISPLAY – Morphine 1 mL Syringe Label
For IM or IV use. 1 mL Single-Dose.

Morphine Sulfate Injection, USP CII

2 mg/mL

Rx only

PACKAGE LABEL

PACKAGE LABEL - PRINCIPAL DISPLAY – Morphine 1 mL Carton Panel
Rx only NDC 76045-005-12
Morphine Sulfate Injection, USP CII
4 mg/mL
For Intramuscular or Intravenous use.

Do NOT place syringe on a Sterile Field.

24 X 1 mL single-dose prefilled syringes

PACKAGE LABEL

PACKAGE LABEL - PRINCIPAL DISPLAY - Morphine 1 mL Blister Pack Label

Rx only NDC 76045-005-02

Morphine Sulfate Injection, USP CII

4 mg/mL

For IM or IV use.

1 mL single-dose prefilled syringe

PACKAGE LABEL

PACKAGE LABEL - PRINCIPAL DISPLAY - Morphine 1 mL Syringe Label

For IM or IV use. 1mL Single-Dose.

Morphine Sulfate Injection, USP CII

4 mg/mL

Rx only

PACKAGE LABEL

PACKAGE LABEL - PRINCIPAL DISPLAY – Morphine 1 mL Carton Panel
Rx only NDC 76045-006-12
Morphine Sulfate Injection, USP CII
5 mg/mL
For Intramuscular or Intravenous use.

Do NOT place syringe on a Sterile Field.

24 X 1 mL single-dose prefilled syringes

PACKAGE LABEL

PACKAGE LABEL - PRINCIPAL DISPLAY – Morphine 1 mL Blister Pack Label
Rx only NDC 76045-006-02
Morphine Sulfate Injection, USP CII
5 mg/mL
For IM or IV use.

1 mL single-dose prefilled syringe

PACKAGE LABEL

PACKAGE LABEL - PRINCIPAL DISPLAY - Morphine 1 mL Syringe Label

For IM or IV use. 1 mL Single-Dose.

Morphine Sulfate Injection, USP CII

5 mg/mL

Rx only

PACKAGE LABEL

PACKAGE LABEL - PRINCIPAL DISPLAY – Morphine 1 mL Carton Panel
Rx only NDC 76045-007-10
Morphine Sulfate Injection, USP CII
8 mg/mL
For Intramuscular or Intravenous use.

Do NOT place syringe on a Sterile Field.

24 X 1 mL single-dose prefilled syringes

PACKAGE LABEL

PACKAGE LABEL - PRINCIPAL DISPLAY – Morphine 1 mL Blister Pack Label
Rx only NDC 76045-007-00
Morphine Sulfate Injection, USP CII
8 mg/mL
For IM or IV use.

1 mL single-dose prefilled syringe

PACKAGE LABEL

PACKAGE LABEL - PRINCIPAL DISPLAY - Morphine 1 mL Syringe Label

For IM or IV use. 1 mL Single-Dose.

Morphine Sulfate Injection, USP CII

8 mg/mL

Rx only

PACKAGE LABEL

PACKAGE LABEL - PRINCIPAL DISPLAY – Morphine 1 mL Carton Panel
Rx only NDC 76045-008-10
Morphine Sulfate Injection, USP CII
10 mg/mL
For Intramuscular or Intravenous use.

Do NOT place syringe on a Sterile Field.

24 X 1 mL single-dose prefilled syringes

PACKAGE LABEL

PACKAGE LABEL - PRINCIPAL DISPLAY – Morphine 1 mL Blister Pack Label
Rx only NDC 76045-008-00
Morphine Sulfate Injection, USP CII
10 mg/mL
For IM or IV use.

1 mL single-dose prefilled syringe

PACKAGE LABEL

PACKAGE LABEL - PRINCIPAL DISPLAY - Morphine 1 mL Syringe Label

For IM or IV use. 1 mL Single-Dose.

Morphine Sulfate Injection, USP CII

10 mg/mL

Rx only